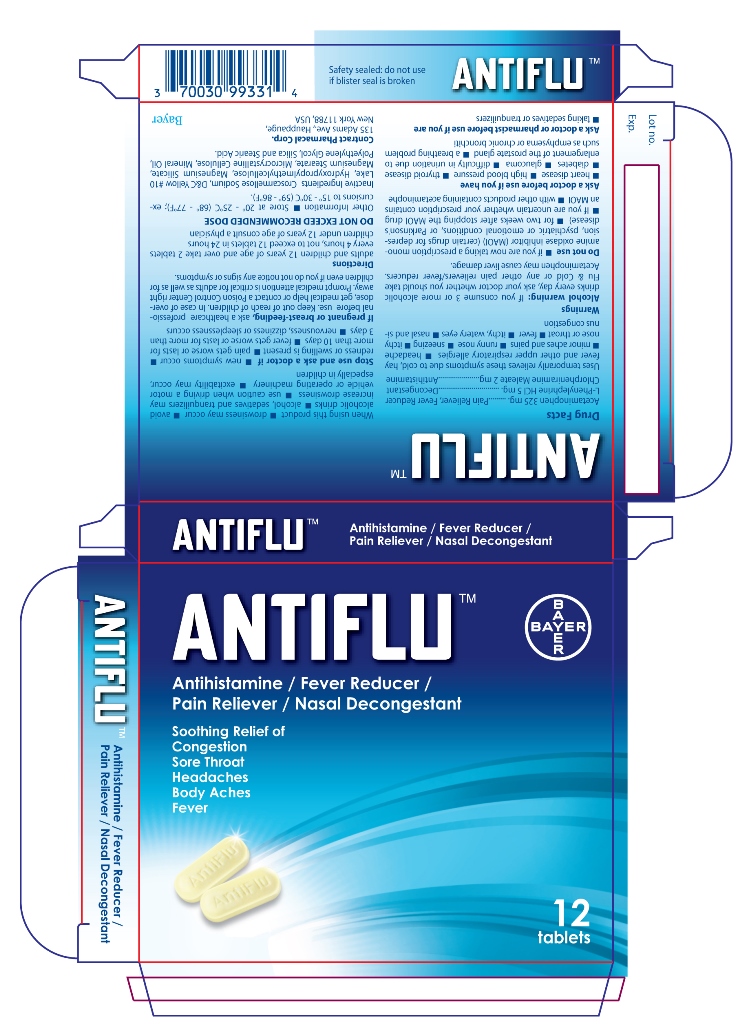 DRUG LABEL: ANTIFLU
NDC: 0280-0044 | Form: TABLET, COATED
Manufacturer: Bayer HealthCare LLC.
Category: otc | Type: HUMAN OTC DRUG LABEL
Date: 20250117

ACTIVE INGREDIENTS: PHENYLEPHRINE HYDROCHLORIDE 5 mg/1 1; CHLORPHENIRAMINE MALEATE 2 mg/1 1; ACETAMINOPHEN 325 mg/1 1
INACTIVE INGREDIENTS: CROSCARMELLOSE SODIUM; D&C YELLOW NO. 10; MAGNESIUM SILICATE; MAGNESIUM STEARATE

Antiflu Fim Coated Tablets